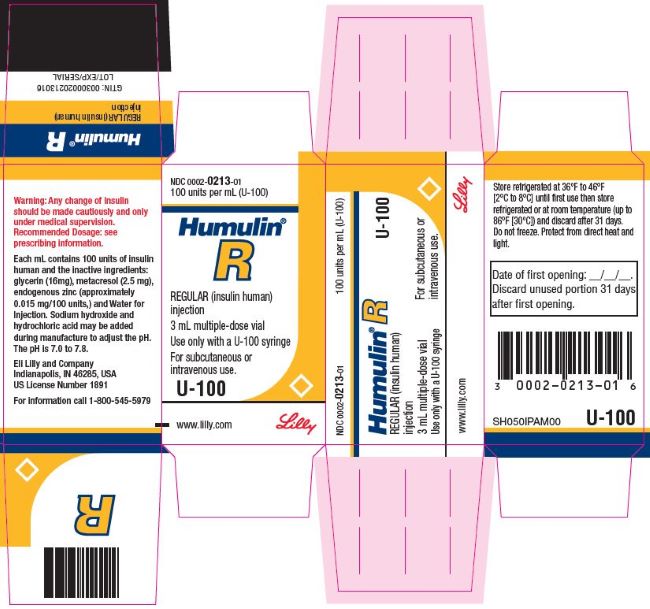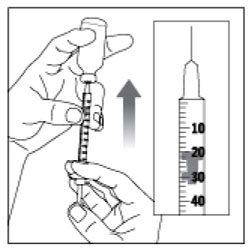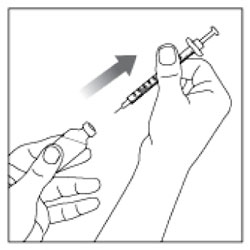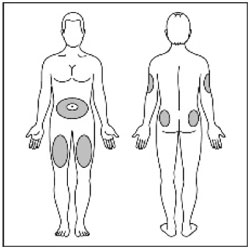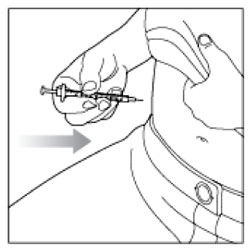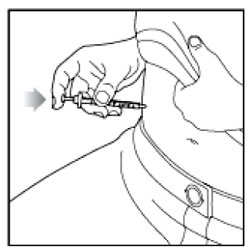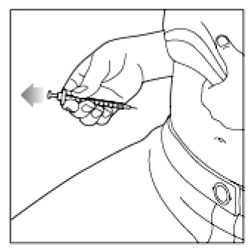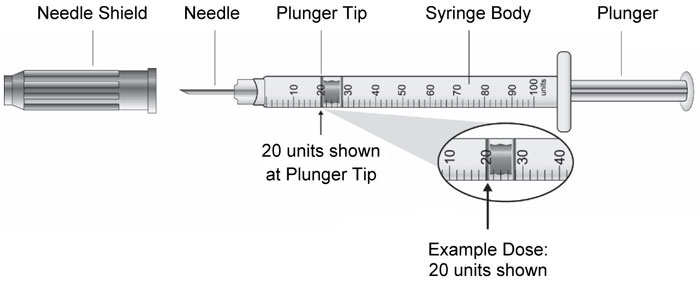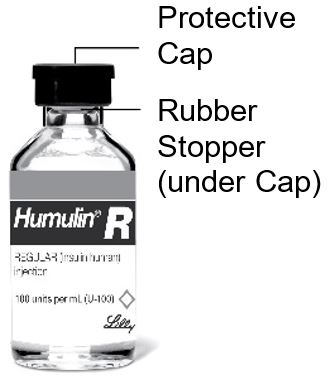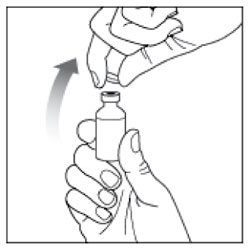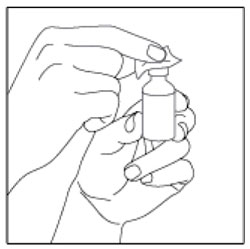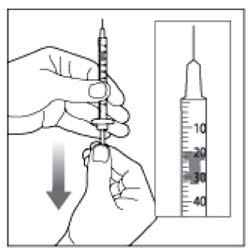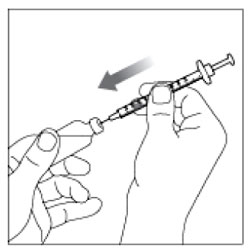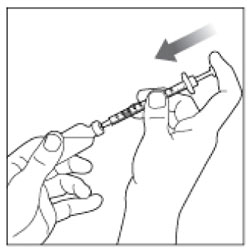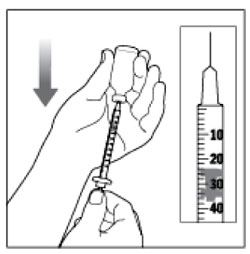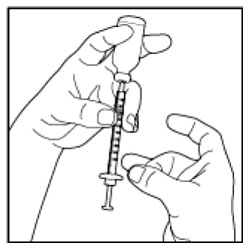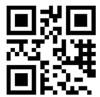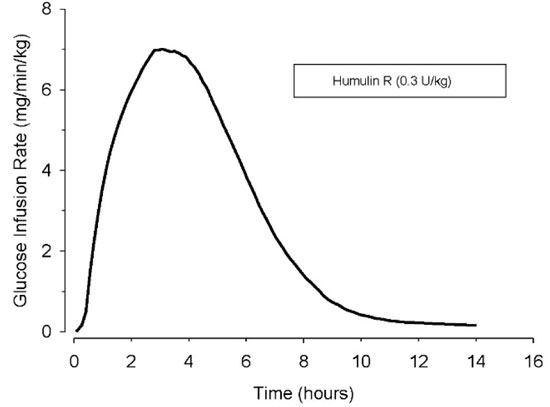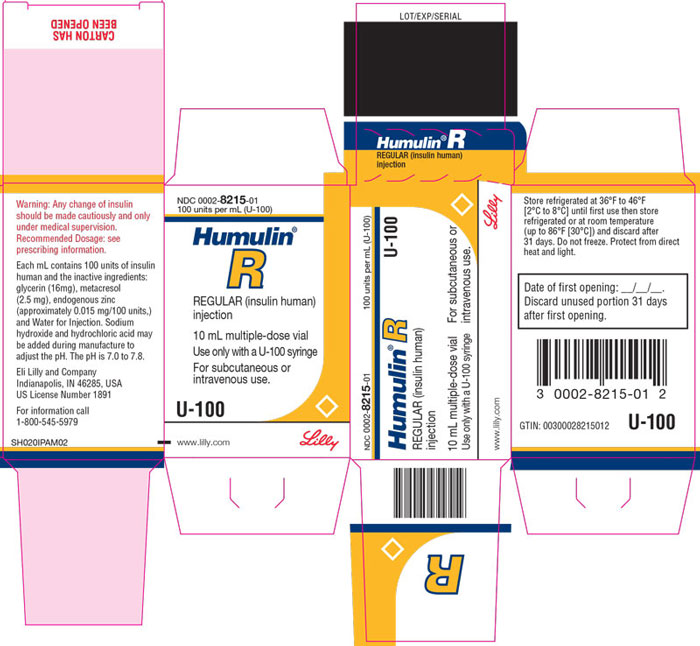 DRUG LABEL: Humulin 
NDC: 0002-8215 | Form: INJECTION, SOLUTION
Manufacturer: Eli Lilly and Company
Category: otc | Type: HUMAN OTC DRUG LABEL
Date: 20250527

ACTIVE INGREDIENTS: insulin human 100 [iU]/1 mL
INACTIVE INGREDIENTS: glycerin 16 mg/1 mL; Metacresol 2.5 mg/1 mL; Zinc 0.015 mg/1 mL; Water; Hydrochloric acid; Sodium hydroxide

HIGHLIGHTS OF PRESCRIBING INFORMATION

These highlights do not include all the information needed to use HUMULIN R safely and effectively. See full prescribing information for HUMULIN R.
HUMULIN R (insulin human) injection, for subcutaneous or intravenous use
Initial U.S. Approval: 1982

1 INDICATIONS AND USAGE

HUMULIN® R is a short-acting human insulin indicated to improve glycemic control in adult and pediatric patients with diabetes mellitus. (1)

2 DOSAGE AND ADMINISTRATION

- See Full Prescribing Information for important administration instructions. (2.1)
- Subcutaneous injection: inject subcutaneously 30 minutes before a meal into the thigh, upper arm, abdomen, or buttocks. Rotate injection sites to reduce risk of lipodystrophy and localized cutaneous amyloidosis. (2.2)
- Intravenous infusion: administer intravenously ONLY under medical supervision at concentrations from 0.1 unit/mL to 1 unit/mL in infusion systems containing 0.9% Sodium Chloride Injection. (2.2)
- Individualize dose based on route of administration, metabolic needs, blood glucose monitoring results and glycemic control goal. (2.3)
- HUMULIN R given by subcutaneous injection should generally be used in regimens with an intermediate- or long-acting insulin. (2.3)
- Do not mix with insulin preparations other than HUMULIN® N. (2.5)

3 DOSAGE FORMS AND STRENGTHS

Injection: 100 units/mL (U-100) is available as:

- 10 mL multiple-dose vial (3)
- 3 mL multiple-dose vial (3)

4 CONTRAINDICATIONS

- Do not use during episodes of hypoglycemia. (4)
- Do not use in patients with hypersensitivity to HUMULIN R or any of its excipients. (4)

5 WARNINGS AND PRECAUTIONS

- Never share needles or syringes with another person. (5.1)
- Hyperglycemia or Hypoglycemia with Changes in Insulin Regimen: Make changes to a patient's insulin regimen (e.g., insulin strength, manufacturer, type, injection site or method of administration) under close medical supervision with increased frequency of blood glucose monitoring. (5.2)
- Hypoglycemia: May be life-threatening. Increase frequency of blood glucose monitoring with changes to: insulin dosage, co-administered glucose lowering medications, meal pattern, physical activity; in patients with renal or hepatic impairment or with hypoglycemia unawareness. (5.3)
- Hypoglycemia Due to Medication Errors: Accidental mix-ups between insulin products can occur. Instruct patients to check insulin labels before injection. (5.4)
- Hypersensitivity Reactions: Severe, life-threatening, generalized allergy, including anaphylaxis, can occur. Discontinue HUMULIN R, monitor, and treat if indicated. (5.5)
- Hypokalemia: May be life-threatening. Monitor potassium levels in patients at risk for hypokalemia and treat if indicated. (5.6)
- Fluid Retention and Heart Failure with Concomitant Use of Thiazolidinediones (TZDs): Observe for signs and symptoms of heart failure; consider dosage reduction or discontinuation if heart failure occurs. (5.7)

6 ADVERSE REACTIONS

Adverse reactions observed with HUMULIN R include hypoglycemia, allergic reactions, injection site reactions, lipodystrophy, weight gain, edema, pruritus, and rash. (6)

To report SUSPECTED ADVERSE REACTIONS, contact Eli Lilly and Company at 1-800-LillyRx (1-800-545-5979) or FDA at 1-800-FDA-1088 or www.fda.gov/medwatch.

7 DRUG INTERACTIONS

- Drugs that Affect Glucose Metabolism: Adjustment of insulin dosage may be needed. (7)
- Antiadrenergic Drugs (e.g., beta-blockers, clonidine, guanethidine, and reserpine): Signs and symptoms of hypoglycemia may be reduced or absent. (5.3, 7)

FULL PRESCRIBING INFORMATION

1 INDICATIONS AND USAGE

HUMULIN R is indicated to improve glycemic control in adult and pediatric patients with diabetes mellitus.

2 DOSAGE AND ADMINISTRATION

2.1 Important Administration Instructions

- Always check the insulin label before administration to confirm the correct insulin product is being used [see Warnings and Precautions (5.4)].
- Inspect HUMULIN R visually before use. It should appear clear and colorless. Do not use HUMULIN R if particulate matter or coloration is seen.

2.2 Route of Administration

Subcutaneous Injection

- Inject HUMULIN R subcutaneously approximately 30 minutes before meals into the thigh, upper arm, abdomen, or buttocks.
- Rotate injection sites within the same region from one injection to the next to reduce the risk of lipodystrophy and localized cutaneous amyloidosis. Do not inject into areas of lipodystrophy or localized cutaneous amyloidosis [see Warnings and Precautions (5.2) and Adverse Reactions (6)].
- HUMULIN R may be diluted with Sterile Diluent for HUMULIN R for subcutaneous injection ONLY under medical supervision.
  - Dilute one part HUMULIN R to nine parts diluent to yield a concentration one-tenth that of HUMULIN R (equivalent to U-10).
  - Dilute one part HUMULIN R to one part diluent to yield a concentration one-half that of HUMULIN R (equivalent to U-50).
  - Diluted HUMULIN R may be used for 28 days when stored at 41°F (5°C) or for 14 days when stored at 86°F (30°C).

Intravenous Administration

- Administer HUMULIN R intravenously ONLY under medical supervision with close monitoring of blood glucose and potassium levels to reduce the risk of hypoglycemia and hypokalemia [see Warnings and Precautions (5.3, 5.6)].
- For intravenous use, HUMULIN R should be used at concentrations from 0.1 unit/mL to 1 unit/mL in infusion systems containing 0.9% Sodium Chloride Injection.
- Intravenous infusion bags prepared with HUMULIN R are stable when stored in a refrigerator (36° to 46°F [2° to 8°C]) for 48 hours and then may be used at room temperature for up to an additional 48 hours.

2.3 Dosing Instructions

- Individualize and adjust the dosage of HUMULIN R based on the route of administration, the patient's metabolic needs, blood glucose monitoring results, and glycemic control goal.
- HUMULIN R given by subcutaneous injection should generally be used in regimens with an intermediate- or long-acting insulin.
- During changes to a patient's insulin regimen, increase the frequency of blood glucose monitoring [see Warnings and Precautions (5.2)].
- Dosage adjustments may be needed with changes in physical activity, changes in meal patterns (e.g., macronutrient content or timing of food intake), changes in renal or hepatic function, or during acute illness [see Warnings and Precautions (5.2, 5.3), Use in Specific Populations (8.6, 8.7)].
- Dosage adjustment may be needed when changing from another insulin to HUMULIN R [see Warnings and Precautions (5.2)].

2.4 Dosage Adjustment due to Drug Interactions

- Dosage adjustment may be needed when HUMULIN R is co-administered with certain drugs [see Drug Interactions (7)].

2.5 Instructions for Mixing with Other Insulins for Subcutaneous Injection

- Do not mix HUMULIN R with insulin preparations other than HUMULIN N.
- To mix HUMULIN R and HUMULIN N, draw HUMULIN R into the syringe first. Inject immediately after mixing.

3 DOSAGE FORMS AND STRENGTHS

Injection: 100 units/mL (U-100), clear and colorless solution available as:

- 10 mL multiple-dose vial
- 3 mL multiple-dose vial

4 CONTRAINDICATIONS

HUMULIN R is contraindicated:

- during episodes of hypoglycemia [see Warnings and Precautions (5.3)]
- in patients with hypersensitivity to HUMULIN R or any of its excipients [see Warnings and Precautions (5.5)]

5 WARNINGS AND PRECAUTIONS

5.1 Never Share Needles or Syringes between Patients

Patients using HUMULIN R vials must never share needles or syringes with another person. Sharing poses a risk for transmission of blood-borne pathogens.

5.2 Hyperglycemia or Hypoglycemia with Changes in Insulin Regimen

Changes in an insulin regimen (e.g., insulin strength, manufacturer, type, injection site or method of administration) may affect glycemic control and predispose to hypoglycemia [see Warnings and Precautions (5.3)] or hyperglycemia. Repeated insulin injections into areas of lipodystrophy or localized cutaneous amyloidosis have been reported to result in hyperglycemia; and a sudden change in the injection site (to an unaffected area) has been reported to result in hypoglycemia [see Adverse Reactions (6)].

Make any changes to a patient's insulin regimen under close medical supervision with increased frequency of blood glucose monitoring. Advise patients who have repeatedly injected into areas of lipodystrophy or localized cutaneous amyloidosis to change the injection site to unaffected areas and closely monitor for hypoglycemia. For patients with type 2 diabetes, adjustments in concomitant anti-diabetic medications may be needed.

5.3 Hypoglycemia

Hypoglycemia is the most common adverse reaction of all insulins, including HUMULIN R. Severe hypoglycemia can cause seizures, may lead to unconsciousness, may be life threatening or cause death. Hypoglycemia can impair concentration ability and reaction time; this may place the patient and others at risk in situations where these abilities are important (e.g., driving or operating other machinery).

Hypoglycemia can happen suddenly and symptoms may differ in each patient and change over time in the same patient. Symptomatic awareness of hypoglycemia may be less pronounced in patients with longstanding diabetes, in patients with diabetic neuropathy, in patients using medications that block the sympathetic nervous system (e.g., beta-blockers) [see Drug Interactions (7)], or in patients who experience recurrent hypoglycemia.

Risk Factors for Hypoglycemia

The risk of hypoglycemia after an injection is related to the duration of action of the insulin and, in general, is highest when the glucose lowering effect of the insulin is maximal. As with all insulins, the glucose lowering effect time course of HUMULIN R may vary in different individuals or at different times in the same individual and depends on many conditions, including the area of injection as well as the injection site blood supply and temperature [see Clinical Pharmacology (12.2)].

Other factors which may increase the risk of hypoglycemia include changes in meal pattern (e.g., macronutrient content or timing of meals), changes in level of physical activity, or changes to concomitant drugs [see Drug Interactions (7)]. Patients with renal or hepatic impairment may be at higher risk of hypoglycemia [see Use in Specific Populations (8.6, 8.7)].

Risk Mitigation Strategies for Hypoglycemia

Patients and caregivers must be educated to recognize and manage hypoglycemia. Self-monitoring of blood glucose plays an essential role in the prevention and management of hypoglycemia. In patients who have reduced symptomatic awareness of hypoglycemia, increased frequency of blood glucose monitoring is recommended.

5.4 Hypoglycemia Due to Medication Errors

Accidental mix-ups between insulin products have been reported. To avoid medication errors between HUMULIN R and other insulins, instruct patients to always check the insulin label before each injection.

5.5 Hypersensitivity Reactions

Severe, life-threatening, generalized allergy, including anaphylaxis, can occur with HUMULIN R [see Adverse Reactions (6)]. If hypersensitivity reactions occur, discontinue HUMULIN R; treat per standard of care and monitor until symptoms and signs resolve. HUMULIN R is contraindicated in patients who have had a hypersensitivity reaction to HUMULIN R or its excipients.

5.6 Hypokalemia

All insulins, including HUMULIN R, cause a shift in potassium from the extracellular to intracellular space, possibly leading to hypokalemia. Untreated hypokalemia may cause respiratory paralysis, ventricular arrhythmia, and death. Monitor potassium levels in patients at risk for hypokalemia if indicated (e.g., patients using potassium-lowering medications, patients taking medications sensitive to serum potassium concentrations).

5.7 Fluid Retention and Heart Failure with Concomitant Use of PPAR-gamma Agonists

Thiazolidinediones (TZDs), which are peroxisome proliferator-activated receptor (PPAR)-gamma agonists, can cause dose-related fluid retention, when used in combination with insulin. Fluid retention may lead to or exacerbate heart failure. Patients treated with insulin, including HUMULIN R, and a PPAR-gamma agonist should be observed for signs and symptoms of heart failure. If heart failure develops, it should be managed according to current standards of care, and discontinuation or dose reduction of the PPAR-gamma agonist must be considered.

6 ADVERSE REACTIONS

The following adverse reactions are also discussed elsewhere in the labeling:

- Hypoglycemia [see Warnings and Precautions (5.3)]
- Hypoglycemia Due to Medication Errors [see Warnings and Precautions (5.4)]
- Hypersensitivity [see Warnings and Precautions (5.5)]
- Hypokalemia [see Warnings and Precautions (5.6)]

Adverse Reactions from Clinical Studies or Postmarketing Reports

The following additional adverse reactions have been identified during clinical studies or from postmarketing reports with use of HUMULIN R. Because some of these reactions are reported voluntarily from a population of uncertain size, it is not always possible to reliably estimate their frequency or to establish a causal relationship to drug exposure.

Adverse reactions associated with insulin initiation and glucose control intensification

Intensification or rapid improvement in glucose control has been associated with a transitory, reversible ophthalmologic refraction disorder, worsening of diabetic retinopathy, and acute painful peripheral neuropathy. Over the long-term, improved glycemic control decreases the risk of diabetic retinopathy and neuropathy.

Hypersensitivity Reactions

Severe allergic reactions may include anaphylaxis, generalized skin reactions, rash, angioedema, bronchospasm, hypotension, and shock.

Hypoglycemia

Hypoglycemia is the most commonly observed adverse reaction in HUMULIN R.

Hypokalemia

HUMULIN R can cause a shift in potassium from the extracellular to intracellular space, possibly leading to hypokalemia.

Injection Site Reactions

Injection site reactions may include injection site hematoma, pain, hemorrhage, erythema, nodules, swelling, discoloration, pruritus, warmth, and injection site mass.

Lipodystrophy

Administration of insulin subcutaneously, including HUMULIN R, has resulted in lipoatrophy (depression in the skin) or lipohypertrophy (enlargement or thickening of tissue) in some patients [see Dosage and Administration (2.2)].

Localized Cutaneous Amyloidosis

Localized cutaneous amyloidosis at the injection site has occurred. Hyperglycemia has been reported with repeated insulin injections into areas of localized cutaneous amyloidosis; hypoglycemia has been reported with a sudden change to an unaffected injection site.

Medication Errors

Medication errors in which other insulins have been accidentally substituted for HUMULIN R have been identified during postapproval use.

Peripheral Edema

Insulins, including HUMULIN R, may cause sodium retention and edema, particularly if previously poor metabolic control is improved by intensified insulin therapy.

Weight Gain

Weight gain can occur with insulins, including HUMULIN R, and has been attributed to the anabolic effects of insulin.

Immunogenicity

As with all therapeutic proteins, insulin administration may cause anti-insulin antibodies to form. The incidence of antibody formation with HUMULIN R is unknown.

7 DRUG INTERACTIONS

Table 1: Clinically Significant Drug Interactions with HUMULIN R
Drugs that May Increase the Risk of Hypoglycemia
Drugs: | Antidiabetic agents, ACE inhibitors, angiotensin II receptor blocking agents, disopyramide, fibrates, fluoxetine, monoamine oxidase inhibitors, pentoxifylline, pramlintide, salicylates, somatostatin analog (e.g., octreotide), and sulfonamide antibiotics
Intervention: | Dose adjustment and increased frequency of glucose monitoring may be required when HUMULIN R is co-administered with these drugs.
Drugs that May Decrease the Blood Glucose Lowering Effect of HUMULIN R
Drugs: | Atypical antipsychotics (e.g., olanzapine and clozapine), corticosteroids, danazol, diuretics, estrogens, glucagon, isoniazid, niacin, oral contraceptives, phenothiazines, progestogens (e.g., in oral contraceptives), protease inhibitors, somatropin, sympathomimetic agents (e.g., albuterol, epinephrine, terbutaline), and thyroid hormones.
Intervention: | Dose adjustment and increased frequency of glucose monitoring may be required when HUMULIN R is co-administered with these drugs.
Drugs that May Increase or Decrease the Blood Glucose Lowering Effect of HUMULIN R
Drugs: | Alcohol, beta-blockers, clonidine, and lithium salts. Pentamidine may cause hypoglycemia, which may sometimes be followed by hyperglycemia.
Intervention: | Dose adjustment and increased frequency of glucose monitoring may be required when HUMULIN R is co-administered with these drugs.
Drugs that May Blunt Signs and Symptoms of Hypoglycemia
Drugs: | Beta-blockers, clonidine, guanethidine, and reserpine
Intervention: | Increased frequency of glucose monitoring may be required when HUMULIN R is co-administered with these drugs.

8 USE IN SPECIFIC POPULATIONS

8.1 Pregnancy

Risk Summary

Available data from published studies over decades have not established an association with human insulin use during pregnancy and major birth defects, miscarriage, or adverse maternal or fetal outcomes (see Data). There are risks to the mother and fetus associated with poorly controlled diabetes in pregnancy (see Clinical Considerations). Animal reproduction studies were not performed.

The estimated background risk of major birth defects is 6-10% in women with pre-gestational diabetes with a HbA1c >7% and has been reported to be as high as 20-25% in women with a HbA1c >10%. The estimated background risk of miscarriage for the indicated population is unknown. In the U.S. general population, the estimated background risk of major birth defects and miscarriage in clinically recognized pregnancies is 2-4% and 15-20%, respectively.

Clinical Considerations

Disease-associated maternal and/or embryo/fetal risk

Poorly controlled diabetes in pregnancy increases the maternal risk for diabetic ketoacidosis, pre-eclampsia, spontaneous abortions, preterm delivery, and delivery complications. Poorly controlled diabetes increases the fetal risk for major birth defects, stillbirth, and macrosomia-related morbidity.

Data

Human Data

While available studies cannot definitively establish the absence of risk, published data from retrospective studies, open-label, randomized, parallel studies and meta-analyses over decades have not established an association with human insulin use during pregnancy and major birth defects, miscarriage, or adverse maternal or fetal outcomes. All available studies have methodological limitations, including lack of blinding, unclear methods or randomization, and small sample size.

8.2 Lactation

Risk Summary

Available data from published literature suggests that exogenous human insulin products, including HUMULIN R, are transferred into human milk. There are no adverse reactions reported in breastfed infants in the literature. There are no data on the effects of exogenous human insulin products, including HUMULIN R on milk production. The developmental and health benefits of breastfeeding should be considered along with the mother's clinical need for HUMULIN R and any potential adverse effects on the breastfed child from HUMULIN R or from the underlying maternal condition.

8.4 Pediatric Use

HUMULIN R is indicated to improve glycemic control in pediatric patients with diabetes mellitus.

The dosage of HUMULIN R must be individualized in pediatric patients based on metabolic needs and frequent monitoring of blood glucose to reduce the risk of hypoglycemia [see Dosage and Administration (2.3), Warnings and Precautions (5.3)].

8.5 Geriatric Use

The effect of age on the pharmacokinetics and pharmacodynamics of HUMULIN R has not been studied. Elderly patients using HUMULIN R may be at increased risk of hypoglycemia due to co-morbid disease [see Warnings and Precautions (5.3)].

8.6 Renal Impairment

The effect of renal impairment on the pharmacokinetics and pharmacodynamics of HUMULIN R has not been studied. Patients with renal impairment are at increased risk of hypoglycemia and may require more frequent HUMULIN R dose adjustment and more frequent blood glucose monitoring [see Warnings and Precautions (5.3)].

8.7 Hepatic Impairment

The effect of hepatic impairment on the pharmacokinetics and pharmacodynamics of HUMULIN R has not been studied. Patients with hepatic impairment are at increased risk of hypoglycemia and may require more frequent HUMULIN R dose adjustment and more frequent blood glucose monitoring [see Warnings and Precautions (5.3)].

10 OVERDOSAGE

Excess insulin administration may cause hypoglycemia and hypokalemia. Mild episodes of hypoglycemia usually can be treated with oral glucose. Adjustments in drug dosage, meal patterns, or exercise may be needed. More severe episodes with coma, seizure, or neurologic impairment may be treated with a glucagon product for emergency use or intravenous glucose. Sustained carbohydrate intake and observation may be necessary because hypoglycemia may recur after apparent clinical recovery. Hypokalemia must be corrected appropriately [see Warnings and Precautions (5.3, 5.6)].

11 DESCRIPTION

Insulin human is produced by recombinant DNA technology utilizing a non-pathogenic laboratory strain of Escherichia coli and has the empirical formula C257H383N65O77S6 with a molecular weight of 5.808 kDa.

HUMULIN R (insulin human) injection is a short-acting human insulin for subcutaneous or intravenous use.

HUMULIN R is a sterile, aqueous, clear, and colorless solution. HUMULIN R contains 100 units of insulin human in each milliliter. Each milliliter of HUMULIN R also contains glycerin (16 mg), metacresol (2.5 mg), endogenous zinc (approximately 0.015 mg/100 units,) and Water for Injection. Sodium hydroxide and hydrochloric acid may be added during manufacture to adjust the pH. The pH is 7.0 to 7.8.

12 CLINICAL PHARMACOLOGY

12.1 Mechanism of Action

The primary activity of insulin, including HUMULIN R, is the regulation of glucose metabolism. Insulin lowers blood glucose by stimulating peripheral glucose uptake, especially by skeletal muscle and fat, and by inhibiting hepatic glucose production. Insulin inhibits lipolysis and proteolysis, and enhances protein synthesis.

12.2 Pharmacodynamics

The time course of insulin action (i.e., glucose lowering) may vary considerably in different individuals or within the same individual. With subcutaneous use, the pharmacologic effect of HUMULIN R begins approximately 30 minutes (range: 10 to 75 minutes) after administration of doses in the 0.05 to 0.4 units/kg range (Figure 1). The effect is maximal at approximately 3 hours (range: 20 minutes to 7 hours) and terminates after approximately 8 hours (range: 3 to 14 hours). In a study that administered 50 and 100 units doses subcutaneously to obese subjects, mean time of termination of effect was prolonged to approximately 18 hours (range approximately 12-24 hours).

Figure 1: Mean Insulin Activity Versus Time Profile After Subcutaneous Injection of HUMULIN R (0.3 unit/kg) in Healthy Subjects.

With intravenous use, the pharmacologic effect of HUMULIN R begins at approximately 10 to 15 minutes and terminates at a median time of approximately 4 hours (range: 2 to 6 hours) after administration of doses in the range of 0.1 to 0.2 units/kg.

The intravenous administration of HUMULIN R was tested in 21 people with type 1 diabetes. During the 6-hour assessment phase patients received intravenous HUMULIN R at an initial dose of 0.5 units/hour, adjusted to maintain blood glucose concentrations near normoglycemia (100 to 160 mg/dL).

The mean blood glucose levels during the assessment phase for patients on HUMULIN R therapy are summarized below in Table 2. All patients achieved near normoglycemia during the 6-hour assessment phase. The average time (± SE) required to attain near normoglycemia was 161 ± 14 minutes for HUMULIN R.

Table 2: Mean Blood Glucose Concentrations (mg/dL) during Intravenous Infusions of HUMULIN R
Time from Start of Infusion (minutes) | Mean Blood Glucose (mg/dL) Intravenousa
0 | 220 ± 11
30 | 204 ± 17
60 | 193 ± 18
120 | 172 ± 28
180 | 153 ± 30
240 | 139 ± 24
300 | 131 ± 22
360 | 128 ± 18
a Results shown as mean ± Standard Deviation.

12.3 Pharmacokinetics

Absorption — In healthy subjects given subcutaneous doses of HUMULIN R ranging from 0.05 to 0.4 unit/kg, mean peak serum levels occurred between 36 to 150 minutes after dosing. After subcutaneous administration of a single 12 unit dose (approximately 0.15 units/kg) to patients with type 1 diabetes, the median peak serum level occurred at approximately 2 hours (range: 20 minutes-6 hours). In a study that administered 50 units (0.4-0.6 unit/kg) and 100 units (0.8-1.3 unit/kg) doses subcutaneously to healthy obese subjects, median peak serum levels were prolonged to approximately 3 hours (range 1 to 8 hours). The absolute bioavailability after a single subcutaneous injection of HUMULIN R ranges from 48% to 89% in the 0.1 to 0.3 unit/kg dose range.

Distribution — When HUMULIN R is administered intravenously at doses of 0.1 or 0.2 unit/kg, the mean volume of distribution ranges between 0.32 to 0.67 L/kg.

Metabolism — The uptake and degradation of insulin occurs predominantly in liver, kidney, muscle, and adipocytes, with the liver being the major organ involved in the clearance of insulin.

Excretion — After subcutaneous administration of HUMULIN R doses in the 0.05-0.4 unit/kg dose range, the median apparent half-life is approximately 1.5 hours (range: 40 minutes-7 hours). Mean apparent half-life of HUMULIN R after subcutaneous administration of higher doses (50 and 100 units) to healthy obese subjects was approximately 3.6 hours (range= 1.6-8.6 hours).

When administered intravenously, HUMULIN R had a mean half-life of approximately 20 minutes at a 0.1 unit/kg dose and 1 hour at a 0.2 unit/kg dose.

13 NONCLINICAL TOXICOLOGY

13.1 Carcinogenesis, Mutagenesis, Impairment of Fertility

Carcinogenicity and fertility studies were not performed in animals.

16 HOW SUPPLIED/STORAGE AND HANDLING

16.1 How Supplied

HUMULIN R injection is 100 units/mL (U-100), a clear and colorless solution available as:

10 mL multiple-dose vial | NDC 0002-8215-01
3 mL multiple-dose vial | NDC 0002-8215-17
3 mL multiple-dose vial | NDC 0002-0213-01

Patients using HUMULIN R vials must never share needles or syringes with another person.

16.2 Storage and Handling

Protect from heat and light. Do not freeze. Do not use HUMULIN R after the expiration date printed on the label or if it has been frozen. See Table 3 below for storage conditions.

Table 3: Storage Conditions HUMULIN R Vialsa
 | Not In-use (Unopened) |  | In-use (Opened)
 | Room Temperature (up to 86°F [30°C]) | Refrigerated (36° to 46°F [2° to 8°C]) | Room Temperature (up to 86°F [30°C]) | Refrigerated (36° to 46°F [2° to 8°C])
10 mL multiple-dose vial 3 mL multiple-dose vial | 31 days | Until expiration date | 31 days | 31 days
a When stored at room temperature, HUMULIN R can only be used for a total of 31 days including both not in-use (unopened) and in-use (opened) storage time.

Storage of Diluted HUMULIN R and Intravenous Infusion Preparations with HUMULIN R

Diluted HUMULIN R for subcutaneous injection may be stored for 28 days when refrigerated at 36° to 46°F [2° to 8°C] or for 14 days at room temperature up to 86°F (30°C) [see Dosage and Administration (2.2)].

Intravenous infusion bags prepared with HUMULIN R may be stored for 48 hours when refrigerated at 36° to 46°F [2° to 8°C]. The prepared intravenous infusion bags may then be stored at room temperature for up to an additional 48 hours [see Dosage and Administration (2.2)].

17 PATIENT COUNSELING INFORMATION

Advise the patient to read the FDA-approved patient labeling (Patient Information and Instructions for Use).

Never Share Needles or Syringes between Patients

Advise patients using HUMULIN R vials not to share needles or syringes with another person. Sharing poses a risk for transmission of blood-borne pathogens.

Hyperglycemia or Hypoglycemia

Inform patients that hypoglycemia is the most common adverse reaction with insulin. Instruct patients on self-management procedures including glucose monitoring, proper injection technique, and management of hypoglycemia and hyperglycemia, especially at initiation of HUMULIN R therapy. Instruct patients on handling of special situations such as intercurrent conditions (illness, stress, or emotional disturbances), an inadequate or skipped insulin dose, inadvertent administration of an increased insulin dose, inadequate food intake, and skipped meals. Instruct patients on the management of hypoglycemia [see Warnings and Precautions (5.3)].

Inform patients that their ability to concentrate and react may be impaired as a result of hypoglycemia. Advise patients who have frequent hypoglycemia or reduced or absent warning signs of hypoglycemia to use caution when driving or operating machinery.

Advise patients that changes in insulin regimen can predispose to hyperglycemia or hypoglycemia and that changes in insulin regimen should be made under close medical supervision [see Warnings and Precautions (5.2)].

Medication Errors

Instruct patients to always check the insulin label before each injection to avoid mix-ups between insulin products [see Warnings and Precautions (5.4)].

Hypersensitivity Reactions

Advise patients that hypersensitivity reactions have occurred with HUMULIN R. Inform patients on the symptoms of hypersensitivity reactions and to seek medical attention if they occur [see Warnings and Precautions (5.5)].

Literature Revised: June 2023

Manufactured by:
Eli Lilly and Company
Indianapolis, IN 46285, USA
US License Number 1891
Copyright © 1997, 2023, Eli Lilly and Company. All rights reserved.

LINR100-0006-USPI-20230620

Humulin R U-100 Vial Patient Package Insert

Patient Information
Humulin® (HU-mu-lin) R
(insulin human)
injection, for subcutaneous or intravenous use
U-100 (100 units/mL)

Do not share your syringes with other people, even if the needle has been changed. You may give other people a serious infection or get a serious infection from them.
What is Humulin R?

- Humulin R is a man-made insulin that is used to control high blood sugar in adults and children with diabetes mellitus.

Who should not use Humulin R?
Do not use Humulin R if you:

- are having an episode of low blood sugar (hypoglycemia).
- have an allergy to human insulin or any of the ingredients in Humulin R. See the end of this Patient Information leaflet for a complete list of ingredients in Humulin R.

What should I tell my healthcare provider before using Humulin R?
Before using Humulin R, tell your healthcare provider about all your medical conditions including, if you:

- have liver or kidney problems.
- take other medicines, especially ones called TZDs (thiazolidinediones).
- have heart failure or other heart problems. If you have heart failure, it may get worse while you take TZDs with Humulin R.
- are pregnant, planning to become pregnant. Talk with your healthcare provider about the best way to control your blood sugar if you plan to become pregnant or while you are pregnant.
- are breast-feeding or plan to breastfeed. HUMULIN R may pass into your breast milk. Talk with your healthcare provider about the best way to feed your baby while using HUMULIN R.

Tell your healthcare provider about all the medicines you take, including prescription and over-the-counter medicines, vitamins, or herbal supplements.
Before you start using Humulin R, talk to your healthcare provider about low blood sugar and how to manage it.

How should I use Humulin R?

- Read the detailed Instructions for Use that comes with your Humulin R.
- Use Humulin R exactly as your healthcare provider tells you to. Your healthcare provider should tell you how much Humulin R to use and when to use it.
- Use Humulin R 30 minutes before eating a meal.
- Know the type, strength, and amount of insulin you use. Do not change the type, or amount of insulin you use unless your healthcare provider tells you to. The amount of insulin and the best time for you to take your insulin may need to change if you use different types of insulin.
- Check your insulin label each time you give your injection to make sure you are using the correct insulin.
- Inject Humulin R under the skin (subcutaneously) of your upper legs (thighs), upper arms, buttocks or stomach area (abdomen). Do not inject Humulin R into your vein (intravenously).
  - Do not mix Humulin R with any other insulin except Humulin® N. If Humulin R is mixed with Humulin N, Humulin R should be drawn into the syringe first. Inject immediately after mixing.
- Change (rotate) your injection sites within the area you choose with each dose to reduce your risk of getting lipodystrophy (pits in skin or thickened skin) and localized cutaneous amyloidosis (skin with lumps) at the injection sites.
  - Do not use the exact same spot for each injection.
  - Do not inject where the skin has pits, is thickened, or has lumps.
  - Do not inject where the skin is tender, bruised, scaly or hard, or into scars or damaged skin.
- Check your blood sugar levels. Ask your healthcare provider what your blood sugars should be and when you should check your blood sugar levels.

Keep Humulin R and all medicines out of reach of children.

Your dose of Humulin R may need to change because of:

- change in level of physical activity or exercise, weight gain or loss, increased stress, illness, change in diet, or because of other medicines you take

What should I avoid while using Humulin R?
While using Humulin R do not:

- drive or operate heavy machinery, until you know how Humulin R affects you.
- drink alcohol or use prescription or over-the-counter medicines that contain alcohol.

What are the possible side effects of Humulin R?
Humulin R may cause serious side effects that can lead to death, including:

- low blood sugar (hypoglycemia). Signs and symptoms of low blood sugar may include:
  - dizziness or lightheadedness, sweating, confusion, headache, blurred vision, slurred speech, shakiness, fast heartbeat, anxiety, irritability or mood changes, hunger.
  - Your healthcare provider may prescribe a glucagon product for emergency use so that others can give you an injection if your blood sugar becomes too low (hypoglycemic) and you are unable to take sugar by mouth.
- severe allergic reaction (whole body reaction). Get medical help right away, if you have any of these signs or symptoms of a severe allergic reaction:
  - a rash over your whole body, have trouble breathing, a fast heartbeat, or sweating.
- low potassium in your blood (hypokalemia).
- heart failure. Taking certain diabetes pills called thiazolidinediones or “TZDs” with Humulin R may cause heart failure in some people. This can happen even if you have never had heart failure or heart problems before. If you already have heart failure, it may get worse while you take TZDs with Humulin R. Your healthcare provider should monitor you closely while you are taking TZDs with Humulin R. Tell your healthcare provider if you have any new or worse symptoms of heart failure including:
  - shortness of breath, swelling of your ankles or feet, sudden weight gain

Treatment with TZDs and Humulin R may need to be adjusted or stopped by your healthcare provider if you have new or worse heart failure.
Get emergency medical help if you have:

- severe hypoglycemia needing hospitalization or emergency room care, and be sure to tell the hospital staff the units of Humulin R that your healthcare provider has prescribed for you.
- trouble breathing, shortness of breath, fast heartbeat, swelling of your face, tongue, or throat, sweating, extreme drowsiness, dizziness, confusion.

The most common side effects of Humulin R include:

- low blood sugar (hypoglycemia), allergic reactions including reactions at your injection site, skin thickening or pits at the injection site (lipodystrophy), weight gain, swelling (edema) in hands or feet, itching and rash.

These are not all of the possible side effects of Humulin R. Call your doctor for medical advice about side effects. You may report side effects to FDA at 1-800-FDA-1088.

General Information about the safe and effective use of Humulin R
Medicines are sometimes prescribed for purposes other than those listed in a Patient Information leaflet. Do not use Humulin R for a condition for which it was not prescribed. Do not give Humulin R to other people, even if they have the same symptoms you have. It may harm them.
This Patient Information leaflet summarizes the most important information about Humulin R. If you would like more information, talk with your healthcare provider. You can ask your pharmacist or healthcare provider for information about Humulin R that is written for healthcare providers. For more information go to www.humulin.com or call 1-800-LillyRx (1-800-545-5979).

What are the ingredients in Humulin R?
Active Ingredient: insulin human
Inactive ingredients: glycerin, metacresol, and Water for Injection as inactive ingredients. Sodium hydroxide and hydrochloric acid may be added to adjust the pH.
Manufactured by: Eli Lilly and Company, Indianapolis, IN 46285, USA
US License Number 1891
For more information about Humulin R go to www.humulin.com.
Copyright © 2007, 2022, Eli Lilly and Company. All rights reserved.

This Patient Information has been approved by the U.S. Food and Drug Administration.

Revised: June 2022

LINR100-0004-PPI-20220627

Humulin R U-100 Vial Instructions for Use

Instructions for Use

Humulin® (HU-mu-lin) R

(insulin human)

injection, for subcutaneous or intravenous use

3 mL or 10 mL multiple-dose vial (100 units/mL)

Read the Instructions for Use before you start taking HUMULIN R and each time you get a new vial. There may be new information. This information does not take the place of talking to your healthcare provider about your medical condition or your treatment.

Do not share your syringes with other people, even if the needle has been changed. You may give other people a serious infection or get a serious infection from them.

Supplies needed to give your injection

- a 3 mL or 10 mL multiple-dose HUMULIN® R vial
- a U-100 insulin syringe and needle
- 2 alcohol swabs
- 1 sharps container for throwing away used needles and syringes. See “Disposing of used needles and syringes” at the end of these instructions.

Vial

Syringe

Preparing the Dose

- Wash your hands with soap and water.
- Check the HUMULIN R label to make sure you are taking the right type of insulin. This is especially important if you use more than 1 type of insulin.
- Do not use HUMULIN R past the expiration date printed on the label or 31 days after you first use it.
- Always use a new syringe or needle for each injection to help make sure the syringe needle is sterile and to prevent blocked needles. Do not reuse or share your syringes or needles with other people. You may give other people a serious infection or get a serious infection from them.

Step 1:
Check the insulin. HUMULIN R solution should look clear and colorless. Do not use HUMULIN R if it looks cloudy, thick, slightly colored, or if you see particles in the solution.

Step 2:
If you are using a new HUMULIN R vial, flip off the plastic protective Cap, but do not remove the Rubber Stopper.

Step 3:
Wipe the Rubber Stopper with an alcohol swab.

Step 4:
Hold the syringe with the needle pointing up. Pull down on the Plunger until the tip of the Plunger reaches the line for the number of units for your prescribed dose.

(Example Dose: 20 units shown)

Step 5:
Push the needle through the Rubber Stopper of the vial.

Step 6:
Push the Plunger all the way in. This puts air into the vial.

Step 7:
Turn the vial and syringe upside down and slowly pull the plunger down until the tip is a few units past the line for your prescribed dose.

(Example Dose: 20 units Plunger is shown at 24 units)

If there are air bubbles in the syringe, tap the syringe gently a few times to let any air bubbles rise to the top.

Step 8:
Slowly push the Plunger up until the tip reaches the line for your prescribed dose.
Check to make sure that you have the right dose.

(Example Dose: 20 units shown)

Step 9:
Pull the syringe out of the vial's Rubber Stopper.

If you use HUMULIN R with HUMULIN N:

- HUMULIN N is the only type of insulin that can be mixed with HUMULIN R. Do not mix HUMULIN R with any other type of insulin.
- HUMULIN R should be drawn up into the syringe first, before you draw up Humulin N. Talk to your healthcare provider if you are not sure about the right way to mix HUMULIN R and HUMULIN N.
- Give your injection right away.

Giving your Injection

- Inject your insulin exactly as your healthcare provider has shown you.
- Change (rotate) your injection sites within the area you choose for each dose to reduce your risk of getting lipodystrophy (pits in skin or thickened skin) and localized cutaneous amyloidosis (skin with lumps) at the injection sites.
- Do not inject where the skin has pits, is thickened, or has lumps.
- Do not inject where the skin is tender, bruised, scaly or hard, or into scars or damaged skin.

Step 10:
Choose your injection site.
HUMULIN R is injected under the skin (subcutaneously) of your stomach area (abdomen), buttocks, upper legs or upper arms.
Wipe the skin with an alcohol swab. Let the injection site dry before you inject your dose.

Step 11:
Insert the needle into your skin.

Step 12:
Push down on the Plunger to inject your dose.
The needle should stay in your skin for at least 5 seconds to make sure you have injected all of your insulin dose.

Step 13:
Pull the needle out of your skin.

- You may see a drop of insulin at the needle tip. This is normal and does not affect the dose you received.
- If you see blood after you take the needle out of your skin, press the injection site with a piece of gauze or an alcohol swab. Do not rub the area.
- Do not recap the needle. Recapping the needle can lead to a needle stick injury.

Disposing of used needles and syringes:

- Put your used needles and syringes in a FDA-cleared sharps disposal container right away after use. Do not throw away (dispose of) loose needles and syringes in your household trash.
- If you do not have a FDA-cleared sharps disposal container, you may use a household container that is:
  - made of a heavy-duty plastic,
  - can be closed with a tight-fitting, puncture-resistant lid, without sharps being able to come out,
  - upright and stable during use,
  - leak resistant, and
  - properly labeled to warn of hazardous waste inside the container.
- When your sharps disposal container is almost full, you will need to follow your community guidelines for the right way to dispose of your sharps disposal container. There may be state or local laws about how you should throw away used needles and syringes. For more information about safe sharps disposal, and for specific information about sharps disposal in the state that you live in, go to the FDA's website at: http://www.fda.gov/safesharpsdisposal.
- Do not dispose of your used sharps disposal container in your household trash unless your community guidelines permit this. Do not recycle your used sharps disposal container.

How should I store HUMULIN R?

All unopened vials:

- Store all unopened vials in the refrigerator at 36° to 46°F (2° to 8°C).
- Do not freeze. Do not use if it has been frozen.
- Keep away from heat and out of direct light.
- Unopened vials can be used until the expiration date on the carton and label, if they have been stored in the refrigerator.
- Unopened vials should be thrown away after 31 days if they are stored at room temperature

After vials have been opened:

- Store opened vials in the refrigerator or at room temperature up to 86°F (30°C) for up to 31 days.
- Keep away from heat and out of direct light.
- Throw away all opened vials after 31 days, even if there is still insulin left in the vial.

General information about the safe and effective use

- Keep HUMULIN R vials, syringes, needles, and all medicines out of the reach of children.
- Always use a new syringe or needle for each injection.
- Do not reuse or share your syringes or needles with other people. You may give other people a serious infection or get a serious infection from them.

If you have any questions or problems with your HUMULIN, contact Lilly at 1-800-Lilly-Rx (1-800-545-5979) or call your healthcare provider for help. For more information on HUMULIN and insulin, go to www.humulin.com.

Scan this code to launch the humulin.com website

This Instructions for Use has been approved by the U.S. Food and Drug Administration.

Humulin® is a trademark of Eli Lilly and Company.

Instructions for Use revised: June 2022

Manufactured by:
Eli Lilly and Company, Indianapolis, IN 46285, USA
US License Number 1891

Copyright © 1997, 2022, Eli Lilly and Company. All rights reserved.

LINR100VL-0004-IFU-20220627

PACKAGE CARTON – HUMULIN R U-100 Vial 10 mL 1ct

NDC 0002-8215-01

100 units per mL (U-100)

Humulin® R

REGULAR (insulin human) injection

10 mL multiple-dose vial

Use only with a U-100 syringe

For subcutaneous or intravenous use.

U-100

www.lilly.com

Lilly

PACKAGE CARTON – HUMULIN R U-100 Vial 3 mL 1ct

NDC 0002-0213-01

100 units per mL (U-100)

Humulin® R

REGULAR (insulin human)
injection

3 mL multiple-dose vial

Use only with a U-100 syringe

For subcutaneous or intravenous use.

U-100

www.lilly.com

Lilly